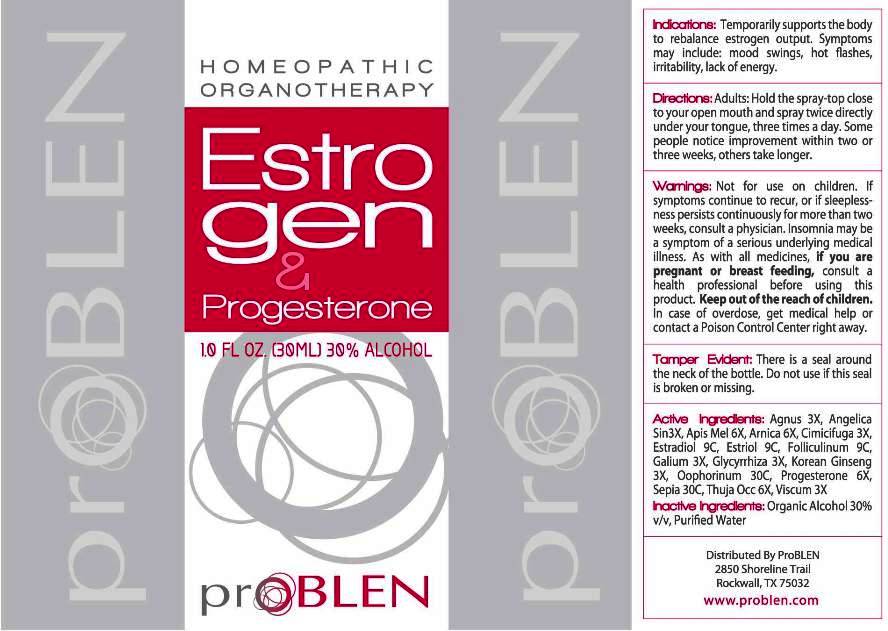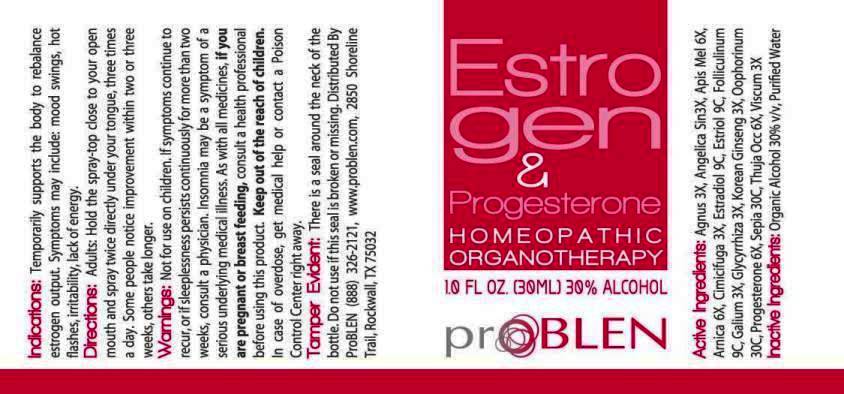 DRUG LABEL: Estrogen and Progesterone
NDC: 43853-0017 | Form: SPRAY
Manufacturer: ProBLEN
Category: homeopathic | Type: HUMAN OTC DRUG LABEL
Date: 20170112

ACTIVE INGREDIENTS: CHASTE TREE 3 [hp_X]/1 mL; ANGELICA SINENSIS ROOT 3 [hp_X]/1 mL; APIS MELLIFERA 6 [hp_X]/1 mL; ARNICA MONTANA 6 [hp_X]/1 mL; BLACK COHOSH 3 [hp_X]/1 mL; ESTRADIOL 9 [hp_C]/1 mL; ESTRIOL 9 [hp_C]/1 mL; ESTRONE 9 [hp_C]/1 mL; GALIUM APARINE 3 [hp_X]/1 mL; GLYCYRRHIZA GLABRA 3 [hp_X]/1 mL; ASIAN GINSENG 3 [hp_X]/1 mL; SUS SCROFA OVARY 30 [hp_C]/1 mL; PROGESTERONE 6 [hp_X]/1 mL; SEPIA OFFICINALIS JUICE 30 [hp_C]/1 mL; THUJA OCCIDENTALIS LEAFY TWIG 6 [hp_X]/1 mL; VISCUM ALBUM FRUITING TOP 3 [hp_X]/1 mL
INACTIVE INGREDIENTS: WATER; ALCOHOL

Drug Facts:

ACTIVE INGREDIENTS:

Agnus Castus 3X, Angelica Sinensis 3X, Apis Mellifica 6X, Arnica Montana 6X, Cimicifuga Racemosa 3X, Estradiol 9C, Estriol 9C, Folliculinum 9C, Galium Aparine 3X, Glycyrrhiza Glabra 3X, Korean Ginseng 3X, Oophorinum (Suis) 30C, Progesterone 6X, Sepia 30C, Thuja Occidentalis 6X, Viscum Album 3X

INDICATIONS:

Temporarily supports the body to rebalance estrogen output. Symptoms may include: mood swings, hot flashes, irritability, lack of energy.

WARNINGS:

Not for use on children.

If symptoms continue to recur, or if sleeplessness persists continuously for more than two weeks, consult a physician. Insomnia may be a symptom of a serious underlying medical illness.

As with all medicines, if you are pregnant or breast feeding, consult a health professional before using this product.

Keep out of the reach of children. In case of overdose, get medical help or contact a Poison Control Center right away.

Tamper Evident. There is a seal around the neck of the bottle. Do not use if this seal is broken or missing.

KEEP OUT OF REACH OF CHILDREN:

Keep out of the reach of children. In case of overdose, get medical help or contact a Poison Control Center right away.

DIRECTIONS:

Adults: Hold the spray-top close to your open mouth and spray twice directly under your tongue, three times a day. Some people notice improvement within two or three weeks, others take longer.

INDICATIONS:

Temporarily supports the body to rebalance estrogen output. Symptoms may include: mood swings, hot flashes, irritability, lack of energy.

INACTIVE INGREDIENTS:

Organic Alcohol 30% v/v, Purified Water

QUESTIONS:

Distributed By ProBLEN
2850 Shoreline Trail,
Rockwall, TX 75032
www.problen.com

PACKAGE LABEL DISPLAY:

HOMEOPATHIC

ORGANOTHERAPY

Estro

gen

&

Progesterone

1.0 FL. OZ. (30ML)

proBLEN